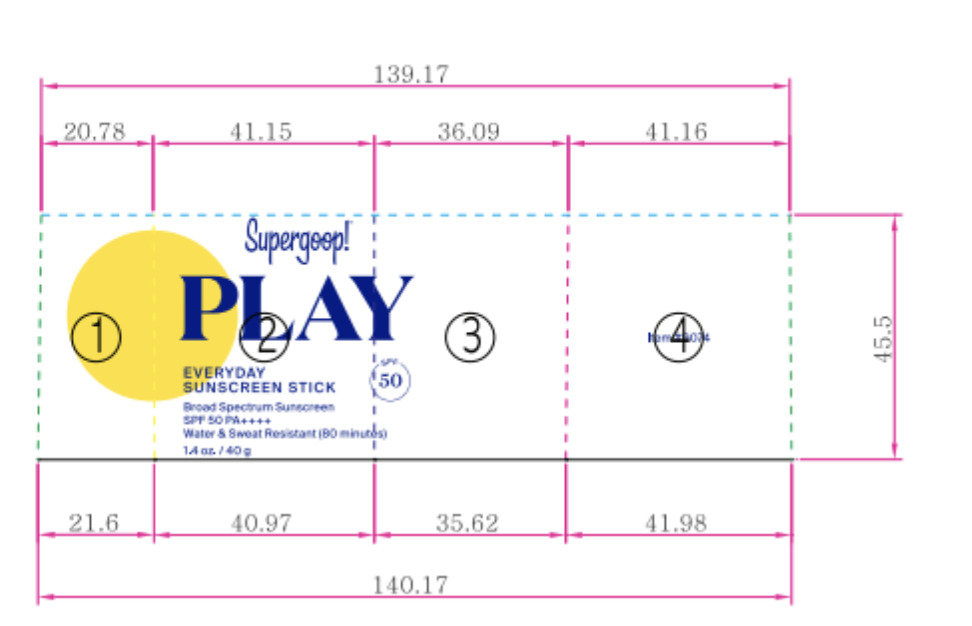 DRUG LABEL: PLAY Sunscreen SPF 50
NDC: 75936-649 | Form: STICK
Manufacturer: Supergoop LLC
Category: otc | Type: HUMAN OTC DRUG LABEL
Date: 20241203

ACTIVE INGREDIENTS: HOMOSALATE 7 g/100 g; OCTOCRYLENE 7 g/100 g; OCTISALATE 5 g/100 g; AVOBENZONE 3 g/100 g
INACTIVE INGREDIENTS: BUTYLOCTYL SALICYLATE; SUNFLOWER OIL; ORANGE TERPENES; POGOSTEMON CABLIN OIL; ETHYLHEXYL PALMITATE; TOCOPHEROL; SILICON DIOXIDE; COCONUT OIL; CITRUS LIMON (LEMON) PEEL OIL; STARCH, TAPIOCA; ANIBA ROSAEODORA WOOD; PARAFFIN; SOYBEAN OIL; OCIMUM BASILICUM (BASIL) OIL; EUCALYPTUS OIL

ACTIVE INGREDIENT

Homosalate 7.0%, Octocrylene 7.0%, Octisalate 5.0%, Avobenzone 3.0%

PURPOSE

Helps prevent sunburn

If used as directed with other sun protection measures (see Directions), decreases the risk of skin cancer and early aging caused by the sun

Keep out of reach of children. If product is swallowed, get medical help, or contact a poison control center right away.

WARNINGS

For External use only

Do not use on damaged or broken skin

When using this product, keep out of eyes. Rinse with water to remove

Stop use and ask a doctor if rash occurs

DOSAGE AND ADMINISTRATION

Apply generously and evenly 15 minutes before sun exposure

Reapply (will vary depending on WR)

after XX minutes of swimming or sweating

Immediately after towel drying

at least every 2 hours

Use a water resistant sunscreen if swimming or sweating

Sun Protection Measures: Spending time in the sun increases your risk of skin cancer and early skin aging. To decrease this risk, regularly use a sunscreen with a Broad Spectrum SPF value of 15 or higher and other sun protection measures including:

Limit time in the sun, especially from 10 a.m.- 2 p.m.

Wear long-sleeved shirts, pants, hats, and sunglasses

Children under 6 months: Ask a doctor

INACTIVE INGREDIENT

Ethylhexyl Palmitate, Synthetic Wax, Tapioca Starch, Butyloctyl Salicylate, Silica, Cocos Nucifera (Coconut) Oil, Helianthus Annuus (Sunflower) Seed Oil, Tocopherol, Orange Oil Terpenes, Eucalyptus Globulus Leaf Oil, Citrus Limon (Lemon) Peel Oil, Pelargonium Graveolens Flower Oil, Glycine Soja (Soybean) Oil, Aniba Rosaeodora (Rosewood) Wood Oil, Pogostemon Cablin Oil, Ocimum Basilicum (Basil) Oil, Limonene.

PACKAGE LABEL

PLAY

Everyday Sunscreen Stick

Broad Spectrum Sunscreen SPF 50 PA++++

Water and Sweat Resistant (80 minutes)

1.4 oz/40g